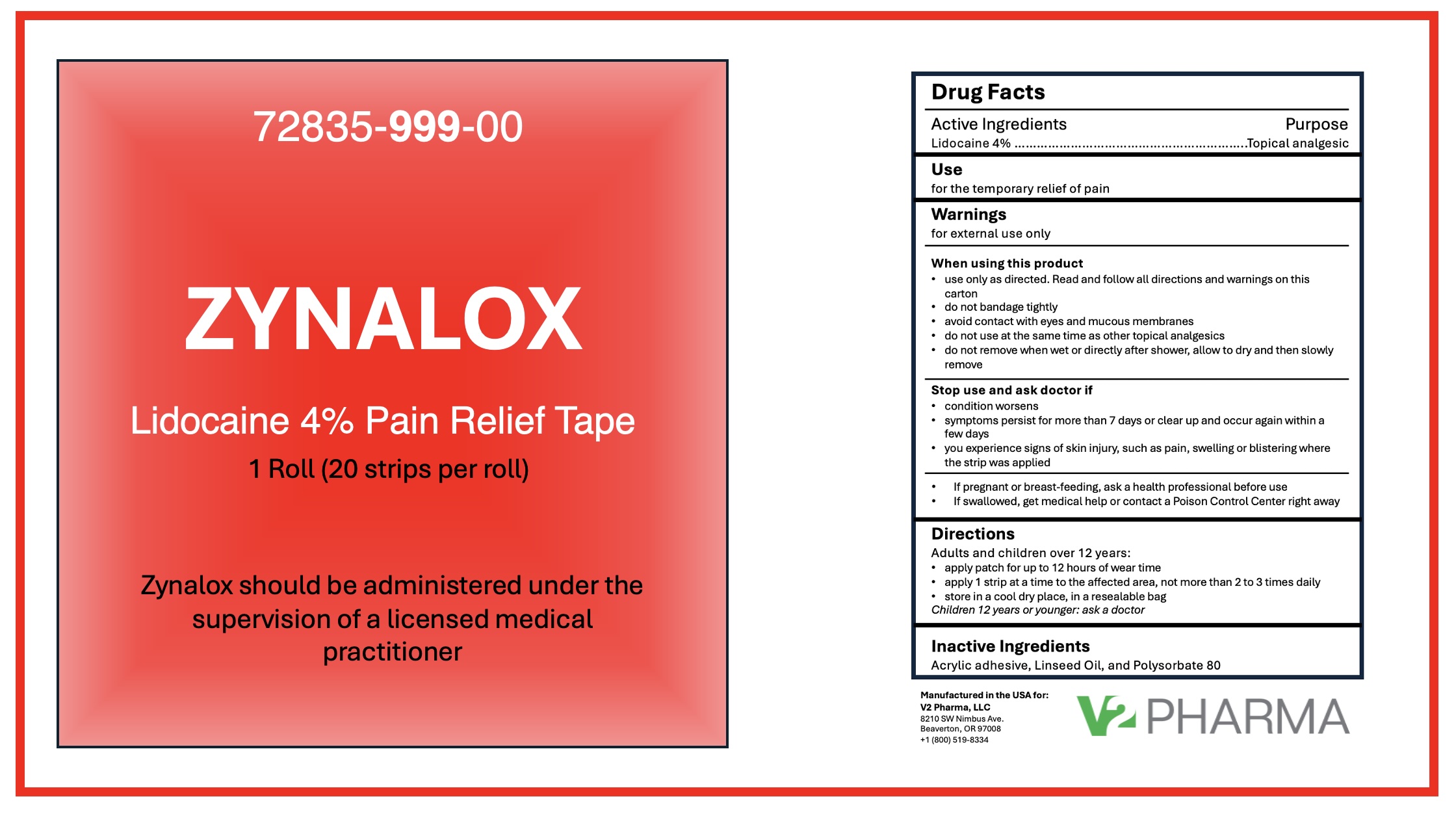 DRUG LABEL: Zynalox Pain Relief Tape
NDC: 72835-999 | Form: TAPE
Manufacturer: V2 Pharma LLC
Category: otc | Type: HUMAN OTC DRUG LABEL
Date: 20251118

ACTIVE INGREDIENTS: LIDOCAINE 4 g/100 1
INACTIVE INGREDIENTS: ACRYLIC ACID; LINSEED OIL; POLYSORBATE 80

Zynalox Pain Relief Tape

Active Ingredients

Lidocaine 4%

Purpose

Topical analgesic

Use

for the temporary relief of pain

Warnings

for external use only
When using this product
• use only as directed. Read and follow all directions and warnings on this package
• do not bandage tightly
• avoid contact with eyes and mucous membranes
• do not use at the same time as other topical analgesics
• do not remove when wet or directly after shower, allow to dry and then slowly remove
Stop use and ask a doctor if
• condition worsens
• symptoms persist for more than 7 days or clear up and occur again within a few days
• you experience signs of skin injury, such as pain, swelling or blistering where the tape was applied
• If pregnant or breast-feeding, ask a health professional before use

KEEP OUT OF REACH OF CHILDREN

• If swallowed, get medical help or contact a Poison Control Center right away

Directions

adults and children over 12 years:
• apply strip for up to 12 hours of wear time
• apply 1 strip at a time to the affected area, not more than 2 to 3 times daily
• store in a cool dry place
children 12 years or younger: ask a doctor

Inactive Ingredients

Acrylic adhesive, Linseed oil, and Polysorbate 80

Manufactured in the USA for V2 Pharma, LLC

Questions/Comments: +1 (800) 519-8334

V2 Pharma, LLC

8210 SW Nimbus Avenue

Beaverton, OR 97008